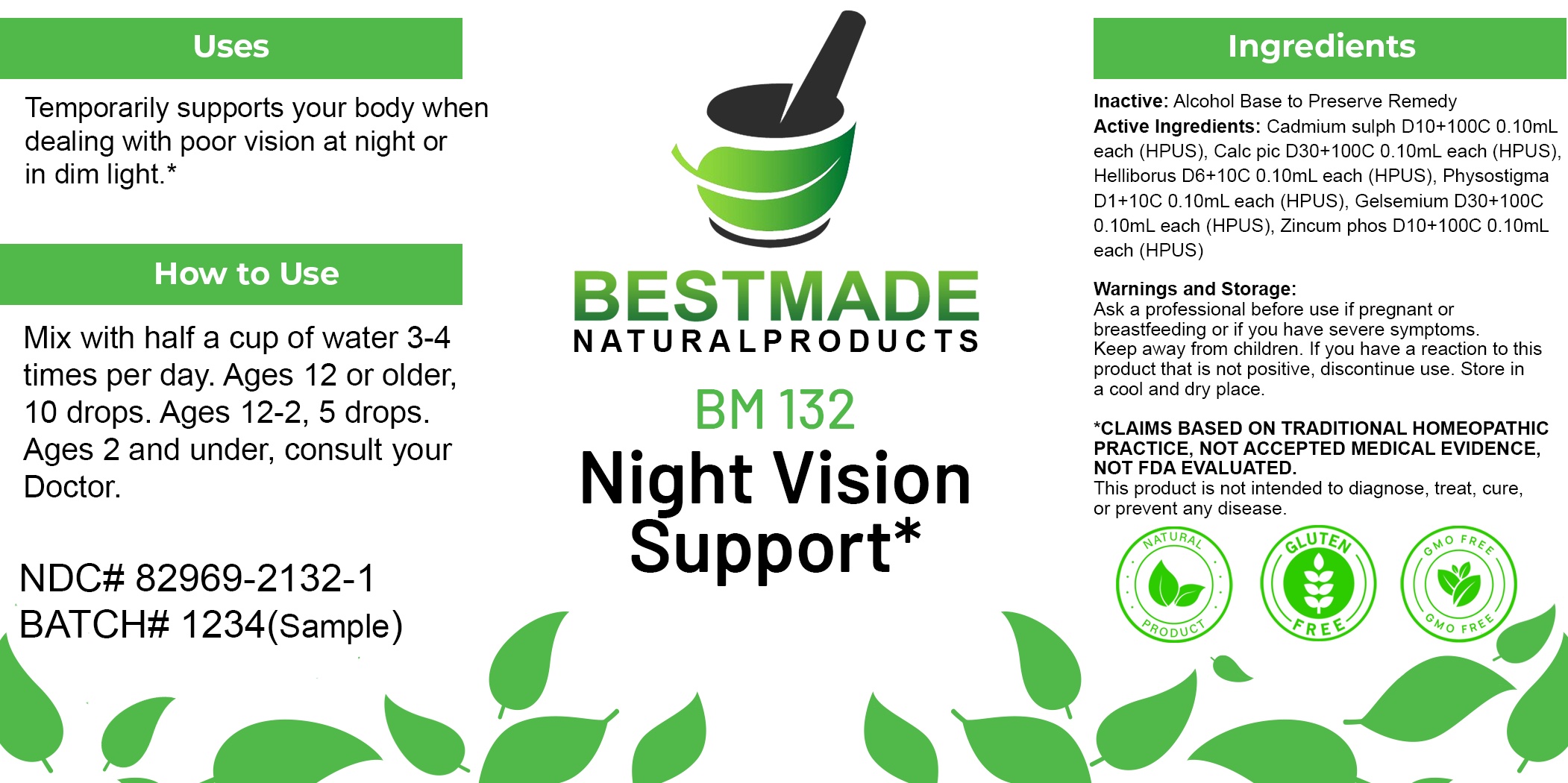 DRUG LABEL: Bestmade Natural Product BM132
NDC: 82969-2132 | Form: LIQUID
Manufacturer: Bestmade Natural Products
Category: homeopathic | Type: HUMAN OTC DRUG LABEL
Date: 20250212

ACTIVE INGREDIENTS: ZINC PHOSPHIDE 30 [hp_C]/30 [hp_C]; CADMIUM SULFIDE 30 [hp_C]/30 [hp_C]; GELSEMIUM SEMPERVIRENS ROOT 30 [hp_C]/30 [hp_C]; PHYSOSTIGMA VENENOSUM SEED 30 [hp_C]/30 [hp_C]; CALCIUM PICRATE 30 [hp_C]/30 [hp_C]; HELLEBORUS NIGER ROOT 30 [hp_C]/30 [hp_C]
INACTIVE INGREDIENTS: ALCOHOL 30 [hp_C]/30 [hp_C]

BM132

DOSAGE AND ADMINISTRATION

How to Use

Mix with half a cup of water 3-4 times per day. Ages 12 or older, 10 drops. Ages 12-2, 5 drops. Ages 2 and under, consult your Doctor.

Inactive:

Alcohol Base to Preserve Product

ACTIVE INGREDIENTS

Cadmium sulph D10+100C 0.10mL each (HPUS), Calc pic D30+100C 0.10mL each (HPUS), Helliborus D6+10C 0.10mL each (HPUS), Physostigma D1+10C 0.10mL each (HPUS), Gelsemium D30+100C 0.10mL each (HPUS), Zincum phos D10+100C 0.10mL each (HPUS)

Uses
Temporarily supports your body when dealing with poor vision at night or in dim light.*

Uses
Temporarily supports your body when dealing with poor vision at night or in dim light.*

KEEP OUT OF REACH OF CHILDREN

Warnings and Storage:

Ask a professional before use if pregnant or breastfeeding or if you have severe symptoms.

Keep away from children. If you have a reaction to this product that is not positive, discontinue use. Store in a cool and dry place

*CLAIMS BASED ON TRADITIONAL HOMEOPATHIC PRACTICE, NOT ACCEPTED MEDICAL EVIDENCE NOT FDA EVALUATED.
This product is not intended to diagnose, treat, cure, or prevent any disease.

Warnings and Storage:

Ask a professional before use if pregnant or breastfeeding or if you have severe symptoms.

Keep away from children. If you have a reaction to this product that is not positive, discontinue use. Store in a cool and dry place

*CLAIMS BASED ON TRADITIONAL HOMEOPATHIC PRACTICE, NOT ACCEPTED MEDICAL EVIDENCE NOT FDA EVALUATED.
This product is not intended to diagnose, treat, cure, or prevent any disease.

Entire package label